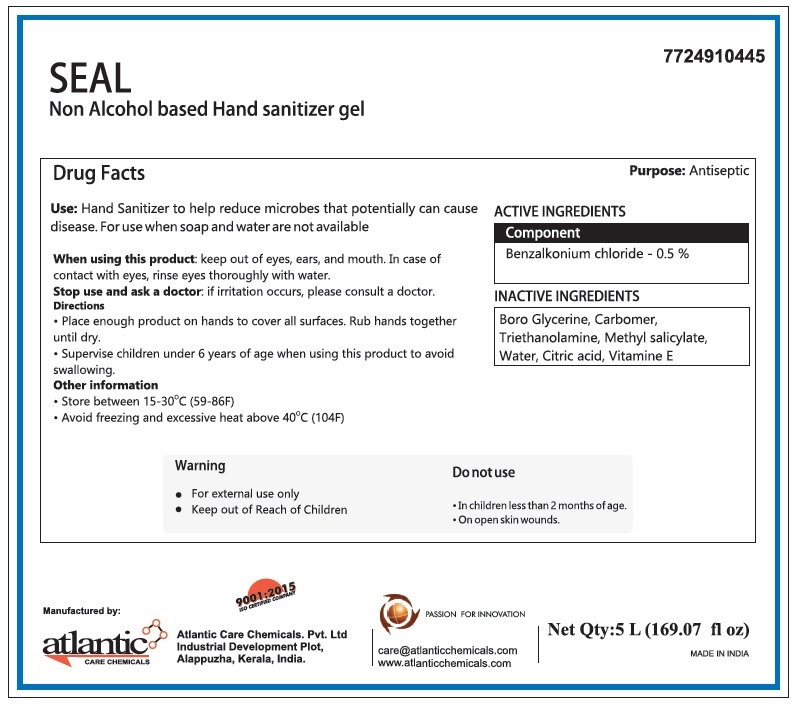 DRUG LABEL: SEAL Non Alcohol based Hand Sanitizer
NDC: 77249-104 | Form: GEL
Manufacturer: ATLANTIC CARE CHEMICALS PRIVATE LIMITED
Category: otc | Type: HUMAN OTC DRUG LABEL
Date: 20200521

ACTIVE INGREDIENTS: BENZALKONIUM CHLORIDE 5 g/1 L
INACTIVE INGREDIENTS: BOROGLYCERIN; CARBOMER HOMOPOLYMER, UNSPECIFIED TYPE; TROLAMINE; METHYL SALICYLATE; WATER; CITRIC ACID MONOHYDRATE; .ALPHA.-TOCOPHEROL

SEAL Non Alcohol based Hand sanitizer gel

Purpose: Antiseptic

ACTIVE INGREDIENTS

Component

Benzalkonium chloride - 0.5 %

INACTIVE INGREDIENTS

Boro Glycerine, Carbomer, Triethanolamine, Methyl salicylate, Water, Citric acid, Vitamine E.

INDICATIONS AND USAGE

Use: Hand Sanitizer to help reduce microbes that potentially can cause disease. For use when soap and water are not available

When using this product: keep out of eyes, ears, and mouth. In case of contact with eyes, rinse eyes thoroughly with water.

Stop use and ask a doctor: if irritation occurs, please consult a doctor.

Do not use

• In children less than 2 months of age

• On open skin wounds.

Warning

• For external use only

• Keep out of Reach of Children

Directions

• Place enough product on hands to cover all surfaces. Rub hands together until dry.

• Supervise children under 6 years of age when using this product to avoid swallowing.

Other information

• Store between 15-30°C (59-86F)

• Avoid freezing and excessive heat above 40°C (104F)

Manufactured by:
Atlantic Care Chemicals. Pvt. Ltd
Industrial Development Plot,
Alappuzha, Kerala, India.

9001:2015

ISO CERTIFIED COMPANY

PASSION FOR INNOVATION

care@atlanticchemicals.com
www.atlanticchemicals.com

MADE IN INDIA